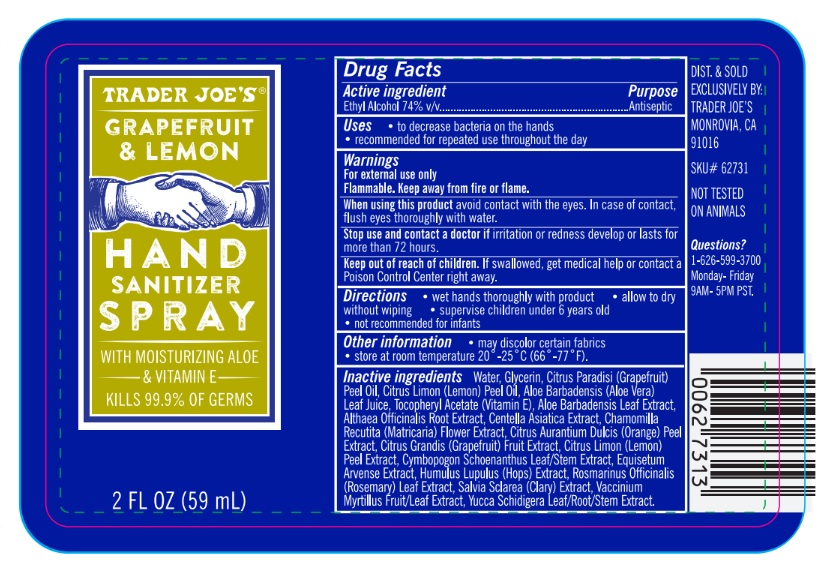 DRUG LABEL: TRADER JOES HAND SANITIZER
NDC: 71270-201 | Form: SPRAY
Manufacturer: Trader Joe's Company
Category: otc | Type: HUMAN OTC DRUG LABEL
Date: 20241022

ACTIVE INGREDIENTS: ALCOHOL 74 mL/100 mL
INACTIVE INGREDIENTS: CENTELLA ASIATICA; CHAMOMILE; ORANGE PEEL; GRAPEFRUIT PEEL; LEMON PEEL; CYMBOPOGON SCHOENANTHUS WHOLE; EQUISETUM ARVENSE WHOLE; HUMULUS LUPULUS WHOLE; ROSMARINUS OFFICINALIS WHOLE; SALVIA SCLAREA WHOLE; VACCINIUM MYRTILLUS WHOLE; YUCCA SCHIDIGERA; WATER; GLYCERIN; GRAPEFRUIT OIL; LEMON OIL; ALOE VERA LEAF; .ALPHA.-TOCOPHEROL ACETATE; ALTHAEA OFFICINALIS ROOT

TRADER JOE'S (as PLD) - HAND SANITIZER SPRAY GRAPEFRUIT & LEMON (71270-201)

ACTIVE INGREDIENT

ETHYL ALCOHOL 74% V/V

PURPOSE

ANTISEPTIC

USES

• for hand washing to decrease bacteria on the skin
• recommended for repeated use throughout the day

WARNINGS

For external use only
Flammable. Keep away from fire or flame.
When using this product avoid contact with the eyes. In case of contact, flush eyes thoroughly with water.
Stop use and contact a doctor if irritation or redness develop or lasts for more than 72 hours.

Keep out of reach of children.

If swallowed, get medical help or contact a Poison Control Center right away.

DIRECTIONS

• wet hands thoroughly with product

• allow to dry without wiping

• supervise children under 6 years old

• not recommended for infants

OTHER INFORMATION

• may discolor certain fabrics
• store at room temperature 20°-25°C (66°-77°F).

INACTIVE INGREDIENTS

Water, Glycerin, Citrus Paradisi (Grapefruit) Peel Oil, Citrus Limon (Lemon) Peel Oil, Aloe Barbadensis (Aloe Vera) Leaf Juice, Tocopheryl Acetate (Vitamin E), Aloe Barbadensis Leaf Extract, Althaea Officinalis Root Extract, Centella Asiatica Extract, Chamomilla Recutita (Matricaria) Flower Extract, Citrus Aurantium Dulcis (Orange) Peel Extract, Citrus Grandis (Grapefruit) Fruit Extract, Citrus Limon (Lemon)
Peel Extract, Cymbopogon Schoenanthus Leaf/Stem Extract, Equisetum Arvense Extract, Humulus Lupulus (Hops) Extract, Rosmarinus Officinalis (Rosemary) Leaf Extract, Salvia Sclarea (Clary) Extract, Vaccinium Myrtillus Fruit/Leaf Extract, Yucca Schidigera Leaf/Root/Stem Extract.